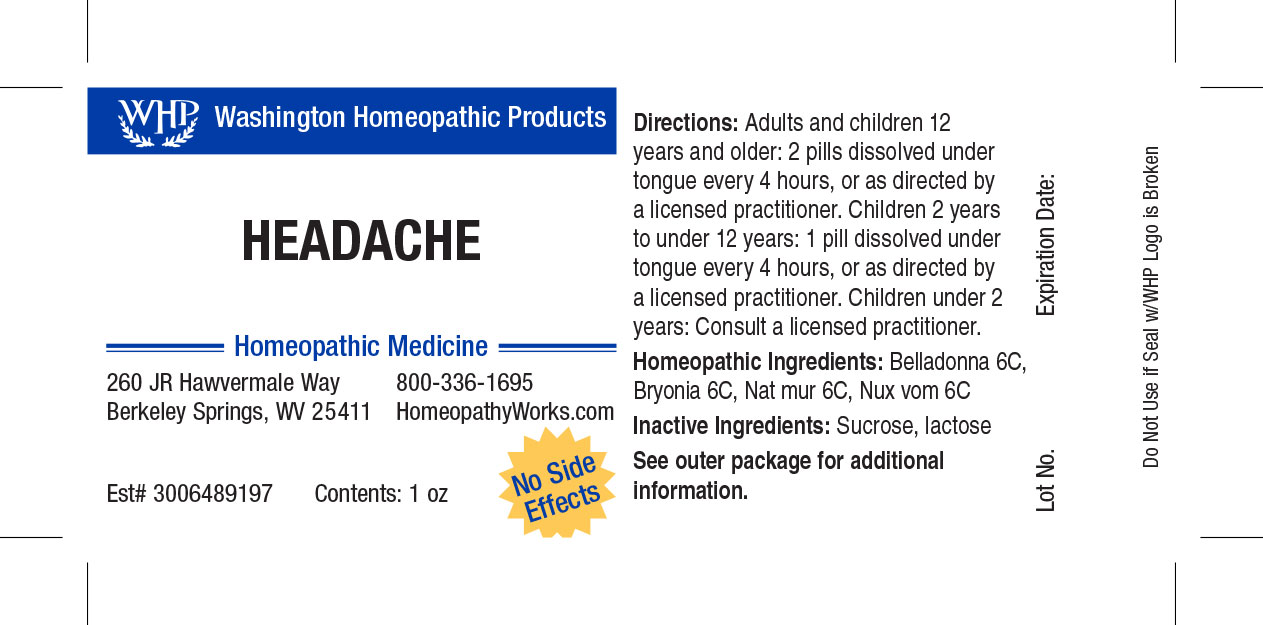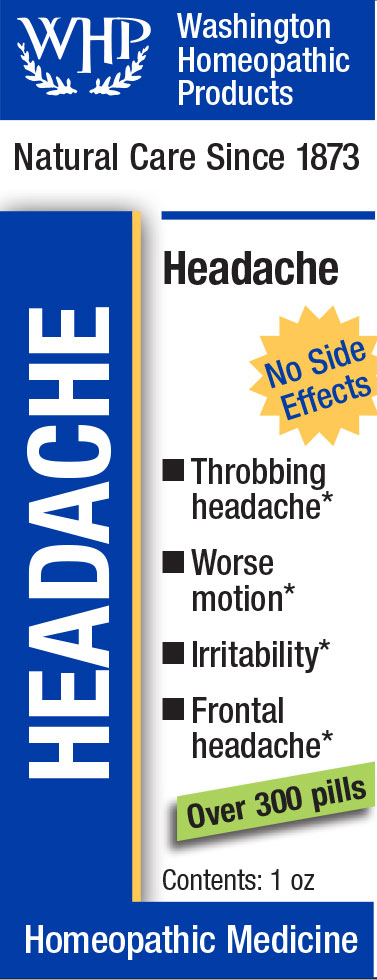 DRUG LABEL: WHP Headache
NDC: 71919-804 | Form: PELLET
Manufacturer: Washington Homeopathic Products
Category: homeopathic | Type: HUMAN OTC DRUG LABEL
Date: 20250128

ACTIVE INGREDIENTS: SODIUM CHLORIDE 6 [hp_C]/1 1; BRYONIA ALBA ROOT 6 [hp_C]/1 1; STRYCHNOS NUX-VOMICA SEED 6 [hp_C]/1 1; ATROPA BELLADONNA 6 [hp_C]/1 1
INACTIVE INGREDIENTS: LACTOSE; SUCROSE

WHP Headache

ACTIVE INGREDIENTS

BELLADONNA 6C

BRYONIA 6C

NAT MUR 6C

NUX VOM 6C

USES

Temporarily relieves headaches.

KEEP OUT OF REACH OF CHILDREN

As with all medications, keep out of reach of children.

INDICATIONS

BELLADONNA Fever

BRYONIA Worse motion

NAT MUR Sneezing

NUX VOM Vomiting

STOP USE AND ASK DOCTOR

If symptoms persist or recur, discontinue use. If pregnant or nursing, consult a licensed practitioner before using this product.

DIRECTIONS

Directions: Adults and children 12 years and older: 2 pills dissolved under tongue every 4 hours, or as directed by a licensed practitioner. Children 4 years to under 12 years: 1 pill dissolved under tongue every 4 hours, or as directed by a licensed practitioner. Children under 4 years: Consult a licensed practitioner.

INACTIVE INGREDIENTS

Sucrose/Lactose